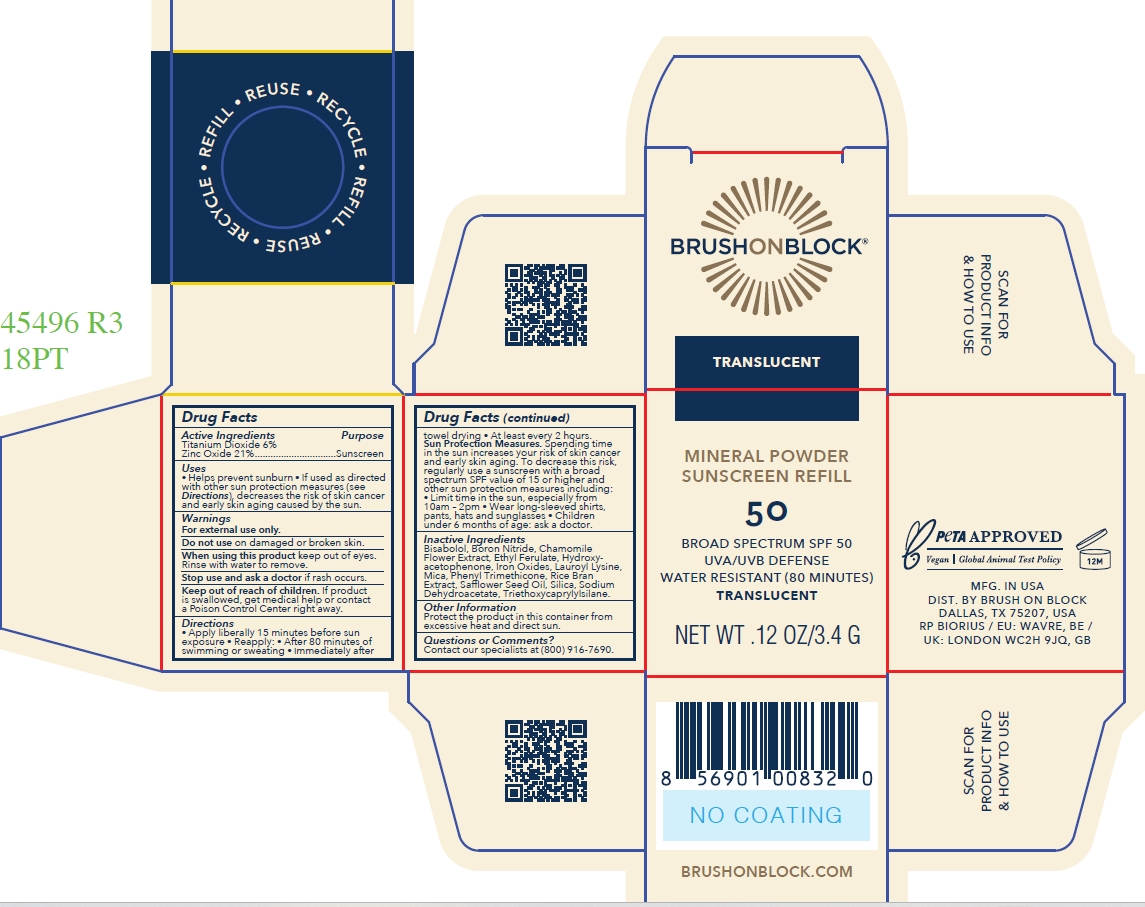 DRUG LABEL: BRUSH ON BLOCK SPF 50 MINERAL TRANSLUCENT ZINC ONLY REFILL
NDC: 58274-025 | Form: POWDER
Manufacturer: SPF Ventures, LLC
Category: otc | Type: HUMAN OTC DRUG LABEL
Date: 20250226

ACTIVE INGREDIENTS: TITANIUM DIOXIDE 6 g/100 g; ZINC OXIDE 21 g/100 g
INACTIVE INGREDIENTS: MICA; PHENYL TRIMETHICONE; LAUROYL LYSINE; BISABOLOL; IRON OXIDES; SODIUM DEHYDROACETATE; SILICA; ETHYL FERULATE; HYDROXYACETOPHENONE; SAFFLOWER SEED OIL POLYGLYCERYL-6 ESTERS; BORON NITRIDE; CHAMAEMELUM NOBILE FLOWER; RICE BRAN; TRIETHOXYCAPRYLYLSILANE

BRUSH ON BLOCK SPF 50 MINERAL POWDER TRANSLUCENT ZINC ONLY REFILL

Active ingredients

ZINC OXIDE 21%

TITANIUM DIOXIDE 6%

Purpose

Sunscreen

Uses

- Helps prevent sunburn
- If used as directed with other sun protection measure (see Directions), decreases the risk of skin cancer and early skin aging caused by the sun.

Warnings

For external use only.

Do not use on damaged or broken skin.

When using this product keep out of eyes. Rinse with water to remove.

Stop use and ask a doctor if rash occurs.

Keep out of reach of children

If product is swallowed, get medical help or contact a Poison Control Center right away.

Directions

- Apply liberally 15 minutes before sun exposure
- Reapply: After 80 minutes of swimming or sweating; Immediately after towel drying; At least every 2 hours;

Sun Protection Measures. Spending time in the sun increases your risk of skin cancer and early skin aging. To decrease this risk, regularly use a sunscreen with a broad spectrum SPF value of 15 or higher and other sun protection measures including: Limit time in the sun, especially from 10am-2pm; Wear long-sleeved shirts, pants, hats and sunglasses; Children under 6 months of age: ask a doctor.

Inactive ingredients

BISABOLOL

BORON NITRIDE

CHAMOMILE FLOWER EXTRACT

ETHYL FERULATE

HYDROXYACETOPHENONE

IRON OXIDES

LAUROYL LYSINE

MICA

PHENYL TRIMETHICONE

RICE BRAN EXTRACT

SAFFLOWER SEED OIL

SILICA

SODIUM DEHYDROACETATE

TRIETHOXYCAPRYLYLSILANE